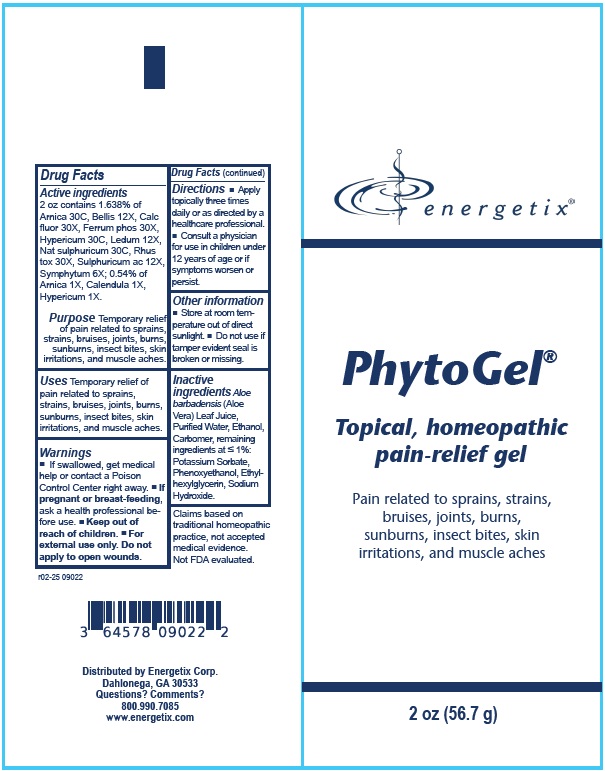 DRUG LABEL: Phytogel
NDC: 64578-0127 | Form: GEL
Manufacturer: Energetix Corporation
Category: homeopathic | Type: HUMAN OTC DRUG LABEL
Date: 20250715

ACTIVE INGREDIENTS: ARNICA MONTANA 1 [hp_X]/1 g; CALENDULA OFFICINALIS FLOWERING TOP 1 [hp_X]/1 g; HYPERICUM PERFORATUM 1 [hp_X]/1 g; BELLIS PERENNIS 12 [hp_X]/1 g; CALCIUM FLUORIDE 30 [hp_X]/1 g; FERRUM PHOSPHORICUM 30 [hp_X]/1 g; LEDUM PALUSTRE TWIG 12 [hp_X]/1 g; SODIUM SULFATE 30 [hp_C]/1 g; TOXICODENDRON PUBESCENS LEAF 30 [hp_X]/1 g; SULFURIC ACID 12 [hp_X]/1 g; COMFREY ROOT 6 [hp_X]/1 g
INACTIVE INGREDIENTS: ALOE VERA LEAF; WATER; CARBOMER HOMOPOLYMER TYPE C (ALLYL PENTAERYTHRITOL CROSSLINKED); PHENOXYETHANOL; ETHYLHEXYLGLYCERIN; POTASSIUM SORBATE; SODIUM HYDROXIDE

PhytoGel

Active ingredients
2 oz contains 1.638% of Arnica 30C, Bellis 12X, Calc fluor 30X, Ferrum phos 30X, Hypericum 30C, Ledum 12X, Nat sulphuricum 30C, Rhus
tox 30X, Sulphuricum ac 12X, Symphytum 6X; 0.54% of
Arnica 1X, Calendula 1X, Hypericum 1X.

Claims based on traditional homeopathic practice, not accepted medical evidence. Not FDA evaluated.

INDICATIONS AND USAGE

UsesTemporary relief of pain related to sprains, strains, bruises, joints, burns, sunburns, insect bites, skin
irritations, and muscle aches.

Warnings

- If swallowed, get medical help or contact a Poison Control Center right away.
- If pregnant or breast feeding,ask a health professional before use.
- For external use only. Do not apply to open wounds.

- Keep out of reach of children.

Directions

- Apply topically three times daily or as directed by a healthcare professional.
- Consult a physician for use in children under 12 years of age or if symptoms worsen or persist.

Other information

- Store at room temperature out of direct sunlight.
- Do not use if tamper evident seal is broken or missing.

INACTIVE INGREDIENT

Inactive ingredientsAloe Barbadensis (Aloe Vera) Leaf Juice, Purified Water, Ethanol, Carbomer, remaining ingredients at ≤ 1%: Potassium Sorbate, Phenoxyethanol, Ethylhexylglycerin, Sodium Hydroxide.

QUESTIONS

Distributed by Energetix Corp.
Dahlonega, GA 30533
Questions? Comments?
800.990.7085
www.energetix.com

PACKAGE LABEL

PhytoGel

Topical, homeopathic pain-relief gel

Pain related to sprains, strains,

bruises, joints, burns,

sunburns, insect bites, skin

irritations, and muscle aches

2 oz (56.7 g)

PURPOSE

PurposeTemporary relief of pain related to sprains, strains, bruises, joints, burns, sunburns, insect bites, skin irritations, and muscle aches